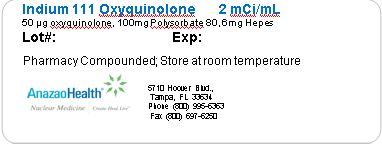 DRUG LABEL: Indium 111 Oxyquinolone
NDC: 51808-126 | Form: SOLUTION
Manufacturer: AnazaoHealth Corporation
Category: prescription | Type: HUMAN PRESCRIPTION DRUG LABEL
Date: 20120619

ACTIVE INGREDIENTS: INDIUM IN-111 OXYQUINOLINE 2 mCi/1 mL
INACTIVE INGREDIENTS: POLYSORBATE 80 100 ug/1 mL; HYDROXYETHYLPIPERAZINE ETHANE SULFONIC ACID 6 mg/1 mL

Indium 111 Oxyquinolone (In-111 Oxine)

DESCRIPTION

This preparation is supplied as a sterile, non-pyrogenic, isotonic aqueous solution with a pH range of 6.5 to 7.5 and is not for direct injection. Each milliliter contains 2 mCi at calibration time, 50μg oxyquinoline, 100μg polysorbate 80, and 6 mg of HEPES (N-2-hydroxyethyl-piperazine-N’-2-ethane sulfonic acid) buffer in 0.75% sodium chloride solution. It is intended for single use only and contains no bacteriostatic agent.

CLINICAL PHARMACOLOGY

Indium forms a saturated (1:3) complex with oxyquinoline. The complex is neutral and lipid-soluble, which enables it to penetrate the cell membrane. Within the cell, indium becomes firmly attached to cytoplasmic components; the liberated oxyquinoline is released by the cell. It is thought that the mechanism of labeling cells with Indium In-111 Oxyquinoline involves an exchange reaction between the oxyquinoline carrier and subcellular components, which chelate indium more strongly than oxyquinoline. The low stability constant of the oxyquinoline complex, estimated at approximately 10, supports this theory.

Following the recommended leukocyte cell labeling procedure, approximately 77% of the added Indium In-111Oxyquinoline is incorporated in the resulting cell pellet (which represents approximately 3-4 x 108 WBC).

Cell clumping can occur and was found in about one fifth of the leukocyte preparations examined. The presence of red blood cells or plasma will lead to reduced leukocyte labeling efficiency. Transferrin in plasma competes for Indium In-111 Oxyquinoline.

Chemotaxis of granulocytes deteriorates during storage and loss of chemotaxis may cause false negative scans. The spontaneous release of Indium In-111 has been reported to range from about 3% at one hour to 24% at 24 hours [ten Berge, R.J.M., Natarajan, A.T., Hardeman, M.R., et al. Labeling with Indium In-111 has detrimental effects on human lymphocytes. Journal of Nuclear Medicine, 24, 615-620 (1983)]. The maximum amount of time recommended between drawing the blood and reinjection should not exceed 5 hours. It is recommended that the labeled cells be used within one hour of preparation, if possible, and no more than three hours after preparation.

Cell aggregates of various degrees have been reported. Cell labeling techniques and standing of cell preparation may be contributing factors.

DECAY CHARACTERISTICS

Indium In-111 decays by electron capture with a physical half-life of 67.2 hours (2.8 days).

Gamma 2 90.2% 171.3 keV

Gamma 3 94 % 245.4 keV

GENERAL

Strict aseptic techniques should be used to maintain sterility throughout the procedures for using this preparation.

Do not use after the expiration time and date (5 days after calibration) stated on the label. The contents of the vial are radioactive. Adequate shielding of the preparation must be maintained at all times.

Indium In-111 Oxyquinoline, like other radioactive drugs, must be handled with care and appropriate safety measures should be used to minimize radiation exposure to clinical personnel. Care should also be taken to minimize radiation exposure to the patient consistent with proper patient management. Radiopharmaceuticals should be used only by physicians who are qualified by training and experience in the safe use and handling of radionuclides and whose experience and training have been approved by the appropriate governmental agency authorized to license the use of radionuclides

DOSAGE AND ADMINISTRATION

The recommended adult (70kg) dose of Indium In-111 Oxyquinoline labeled autologous leukocytes is 7.4 to 18.5 MBq (200-500 μCi). Indium In-111 Oxyquinoline solution is intended for radiolabeling of autologous leukocytes. The Indium In-111 Oxyquinoline labeled autologous leukocytes are administered intravenously.

Imaging is recommended at approximately 24 hours post injection. Typically, anterior and posterior views of the chest, abdomen and pelvis should be obtained with other views as required. Aseptic procedures and a shielded syringe should be employed in the withdrawal of Indium In-111 Oxyquinoline from the vial. Similar procedures should be employed during the labeling procedure and the administration of the labeled leukocytes to the patient. The user should wear waterproof gloves during the entire procedure. The patient’s dose should be measured by a suitable radioactivity calibration system immediately before administration. At this time, the leukocyte preparation should be checked for gross clumping and red blood cell contamination

Storage and Handling

Indium In-111 Oxyquinoline solution should be stored at room temperature (15-25ºC, 59-77ºF)

LABELING PROCEDURES

Sterile technique must be used throughout. It is important that all equipment used for the preparation of reagents be thoroughly cleaned to assure the absence of trace metal impurities. The user should wear waterproof gloves during the handling and administration procedure

1. Withdraw from the patient 30-50 ml blood [preferably fifty (50) ml] using aseptic venipuncture technique using the 60 ml syringe fitted with a 19-gauge or 20-gauge needle and containing approximately 1000-1500 units heparin in 1-2 ml. Blood withdrawal should be smooth and slow so as not to produce bubbles or foaming
2. Remove and dispose of the needle and replace with syringe cap. Gently mix the contents of the syringe and label with the patient’s ID, date and time.
3. Upon receipt of the full syringe for processing, the contents should again be gently mixed.
4. Clamp the syringe barrel to the ring stand in an upright (needle side up) position and tilt the syringe 10-20 degrees from its position perpendicular to the bench.
5. Allow the red cells to sediment 30-60 minutes, depending upon when the supernatant [Leukocyte Rich Plasma (LRP)] looks clear of red cells.
6. Replace the syringe cap with an infusion set
7. Collect the plasma (LRP) in the centrifuge tube marked “WBC” by expressing the LRP through the catheter tubing making sure not to get any red cells into the WBC tube
8. Immediately centrifuge the capped WBC tube at 400-450 g for 5 minutes
9. Transfer the supernatant to the leukocyte poor plasma “LPP” tube leaving behind 0.5-1.0 ml supernatant to cover the white cell button. (Note: the button often contains a small number of red cells and may appear red.)
10. Wash the white cell button with 4-6 ml Sodium Chloride (0.9%) Injection USP. Resuspend the cells by gentle swirling.
11. Centrifuge the capped “WBC” tube at 400-450 g for 5 minutes (alternatively, 150 g for 8 minutes) and discard all but 0.5-1.0 ml of the supernatant to cover the cells.
12. Add 5.0 ml Sodium Chloride (0.9%) Injection USP. Resuspend cells by gentle swirling.
13. With the shielded syringe, draw up approximately 22.2 MBq (600 μCi) Indium In-111 Oxyquinoline. Check the amount of radioactivity in a dose calibrator set for Indium In-111 and record for labeling efficiency calculations. Parenteral drug preparations should be inspected visually for particulate matter and discoloration before administration.
14. In several additions, add the Indium In-111 Oxyquinoline to the “WBC” tube, gently swirling after each addition.
15. Set the lab timer for 15 minutes and allow the capped “WBC” tube to incubate. Swirl the cell preparation several times during the incubation.
16. With a sterile plastic syringe, add half of the saved LPP (or about 8 ml) from the LPP tube. Cap and gently swirl the contents of “WBC” tube to resuspend the cells
17. Centrifuge the “WBC” tube at 450 g for 5 minutes (or 150 g for 8 minutes). Decant supernatant into the “Wash” tube leaving behind about 0.5 ml of the supernate to cover the cells.
18. Assay the activity in the “WBC” tube and in the “Wash” tube in a dose calibrator and record.
19. With a sterile plastic syringe add the remaining LPP to the cell button and gently resuspend by swirling. With a sterile syringe fitted with a 19-gauge needle, resuspend the cells by drawing the cells up into the syringe and expressing the suspension against the tube gently one or twice. Alternatively, draw up the cells into a syringe fitted with the filtered 19-gauge needle, and replace the needle with an unfiltered 19- or 20-gauge needle.
20. . Reserve in the “WBC” tube a minimum amount of white cell suspension for a WBC count. A microscopic examination should also be completed to observe for clumping. Draw up the patient’s dose 7.4 to 18.5 MBq (200-500 μCi) and check the syringe in the dose calibrator. Record the measurement

QUALITY CONTROL

It is generally advantageous to record any observations of cell abnormalities (e.g. cell clumping). A trypan blue exclusion test may also be performed.

PACKAGE LABEL.PRINCIPAL DISPLAY PANEL

Figure 1